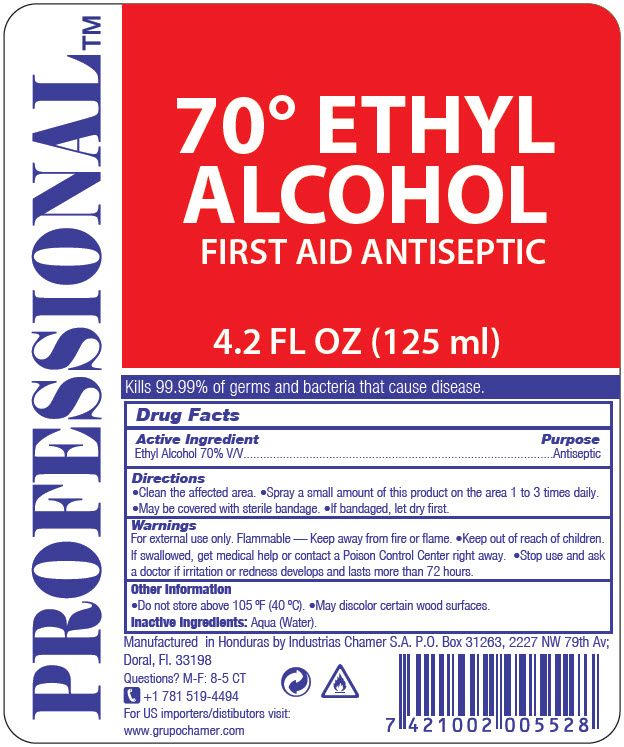 DRUG LABEL: Professional
NDC: 51774-008 | Form: LIQUID
Manufacturer: INDUSTRIAS CHAMER S.A. DE C.V.
Category: otc | Type: HUMAN OTC DRUG LABEL
Date: 20200902

ACTIVE INGREDIENTS: Alcohol 70 mL/100 mL
INACTIVE INGREDIENTS: WATER

Professional™

Drug Facts

Active Ingredient

Ethyl Alcohol 70% V/V

Purpose

Antiseptic

Directions

INDICATIONS AND USAGE

- Clean the affected area.
- Spray a small amount of this product on the area 1 to 3 times daily.
- May be covered with sterile bandage.
- If bandaged, let dry first.

Warnings

For external use only. Flammable — Keep away from fire or flame.

- Keep out of reach of children. If swallowed, get medical help or contact a Poison Control Center right away.

- Stop use and ask a doctor if irritation or redness develops and lasts more than 72 hours.

Other Information

- Do not store above 105 ºF (40 ºC).
- May discolor certain wood surfaces.

Inactive Ingredients

Aqua (Water).

Questions?

M-F: 8-5 CT
+1 781 519-4494

PRINCIPAL DISPLAY PANEL - 125 ml Bottle Label

PROFESSIONAL™

70° ETHYL
ALCOHOL
FIRST AID ANTISEPTIC

4.2 FL OZ (125 ml)